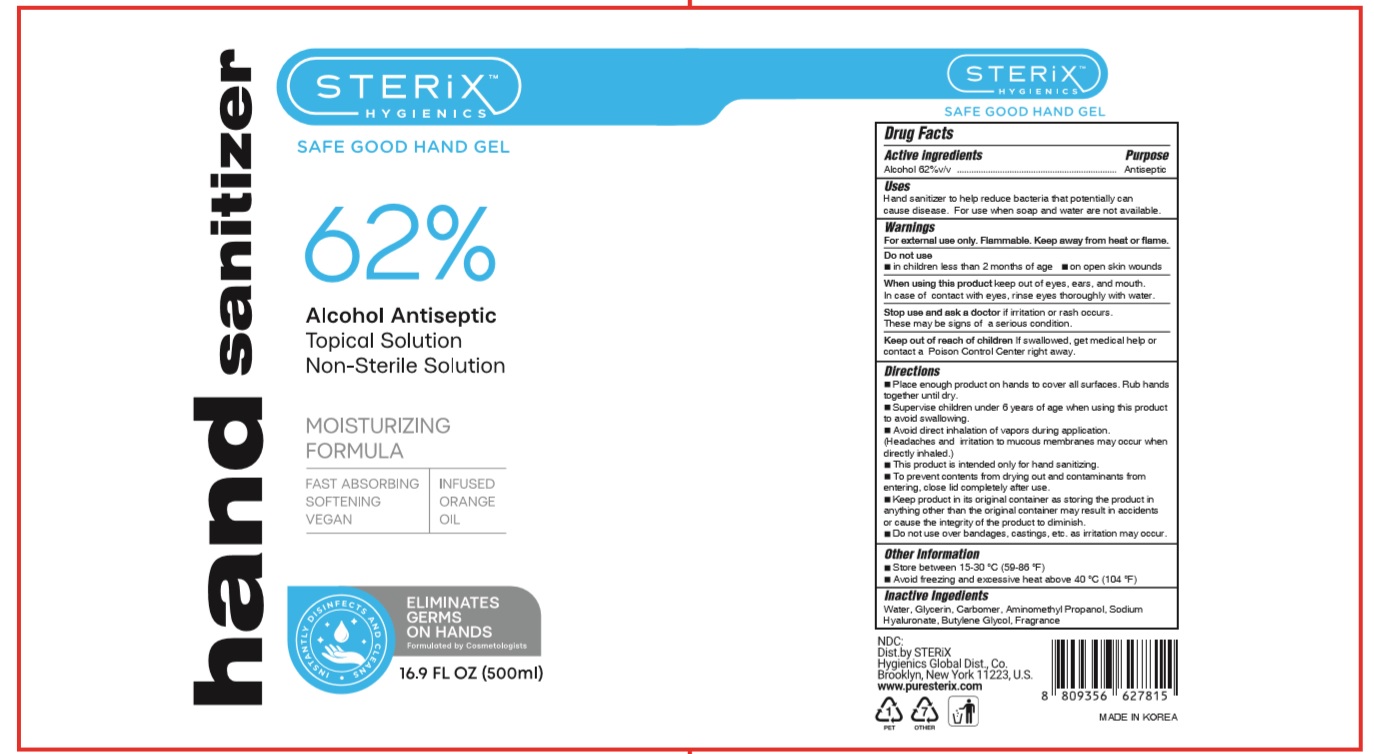 DRUG LABEL: STERIX SAFE GOOD HAND Gel
NDC: 74339-6216 | Form: GEL
Manufacturer: PL COSMETIC
Category: otc | Type: HUMAN OTC DRUG LABEL
Date: 20200512

ACTIVE INGREDIENTS: ALCOHOL 310 mL/500 mL
INACTIVE INGREDIENTS: GLYCERIN; CARBOMER HOMOPOLYMER, UNSPECIFIED TYPE; WATER; BUTYLENE GLYCOL; HYALURONATE SODIUM; AMINOMETHYLPROPANOL

STERIX SAFE GOOD HAND Gel 500 ml Bottle pump 74339-6216-1